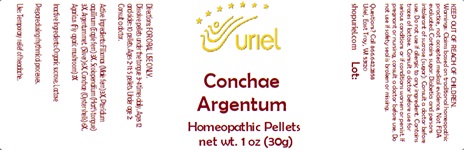 DRUG LABEL: Conchae Argentum
NDC: 48951-3118 | Form: PELLET
Manufacturer: Uriel Pharmacy Inc.
Category: homeopathic | Type: HUMAN OTC DRUG LABEL
Date: 20241210

ACTIVE INGREDIENTS: DRYOPTERIS FILIX-MAS ROOT 3 [hp_X]/1 1; PTERIDIUM AQUILINUM WHOLE 3 [hp_X]/1 1; ASPLENIUM SCOLOPENDRIUM TOP 3 [hp_X]/1 1; SILVER 6 [hp_X]/1 1; OSTREA EDULIS SHELL 6 [hp_X]/1 1; AMANITA MUSCARIA FRUITING BODY 7 [hp_X]/1 1
INACTIVE INGREDIENTS: LACTOSE; SUCROSE

Conchae Argentum

INDICATIONS AND USAGE

Directions: FOR ORAL USE ONLY.

DOSAGE AND ADMINISTRATION

Dissolve pellets under the tongue 3-4 times daily. Ages 12 and older: 10 pellets. Ages 2-11: 5 pellets. Under age 2: Consult a doctor.

ACTIVE INGREDIENT

Active Ingredients: Filix mas (Male fern) 3X, Pteridium aquilinum (Eagle fern) 3X, Scolopendrium (Hart’s tongue) 3X, Argentum met. (Silver) 6X, Conchae (Oyster shells) 6X, Agaricus (Fly agaric mushroom) 7X

Inactive Ingredients: Organic sucrose, Lactose

Prepared using rhythmical processes.

PURPOSE

Use: Temporary relief of headache.

KEEP OUT OF REACH OF CHILDREN.

WARNINGS

Warnings: Claims based on traditional homeopathic practice, not accepted medical evidence. Not FDA evaluated. Contains sugar. Diabetics and persons intolerant of sucrose (sugar): Consult a doctor before use. Do not use if allergic to any ingredient. Contains traces of lactose. Consult a doctor before use for serious conditions or if conditions worsen or persist. If pregnant or nursing, consult a doctor before use. Do not use if safety seal is broken or missing.

Questions? Call 866.642.2858
Uriel, East Troy, WI 53120
shopuriel.com Lot: